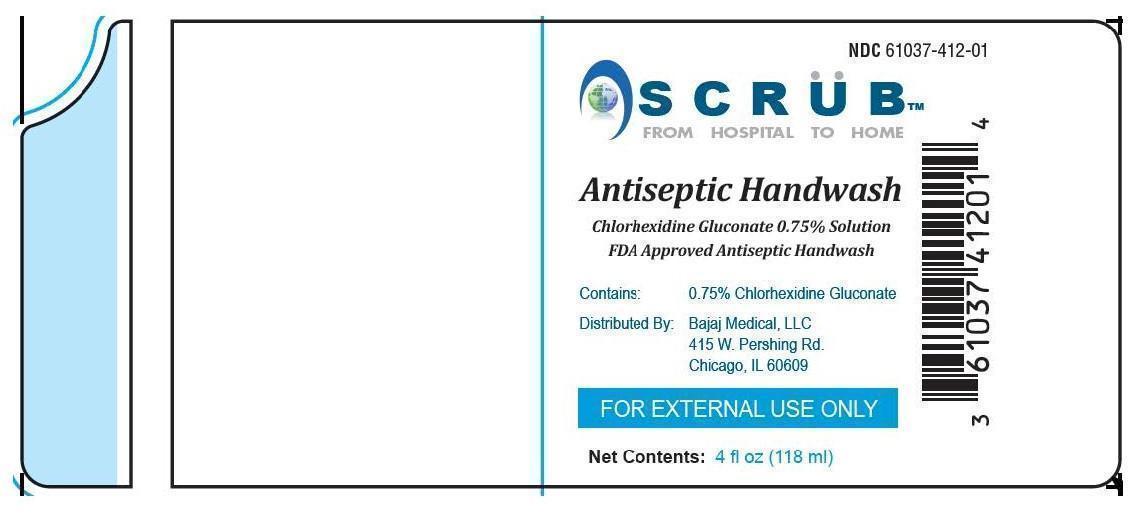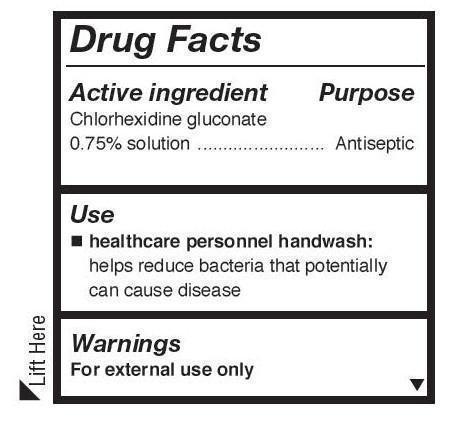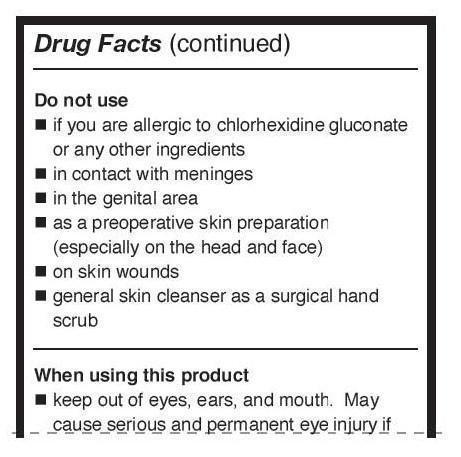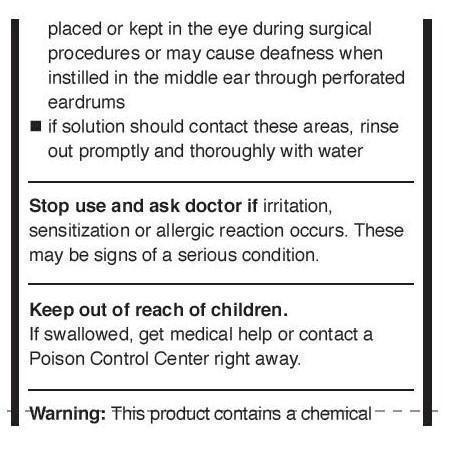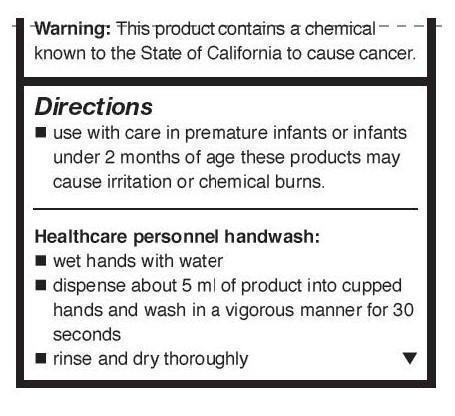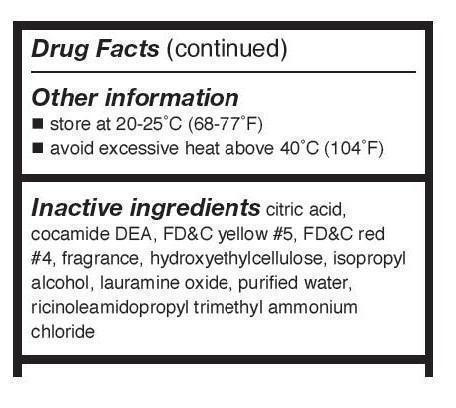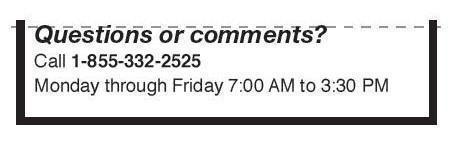 DRUG LABEL: Scrub
NDC: 61037-412 | Form: SOLUTION
Manufacturer: Bajaj Medical, LLC
Category: otc | Type: HUMAN OTC DRUG LABEL
Date: 20141026

ACTIVE INGREDIENTS: CHLORHEXIDINE GLUCONATE .75 mg/100 mL
INACTIVE INGREDIENTS: COCO DIETHANOLAMIDE; HYDROXYETHYL CELLULOSE (140 CPS AT 5%); ISOPROPYL ALCOHOL; LAURAMINE OXIDE; RICINOLEAMIDOPROPYLTRIMONIUM CHLORIDE; WATER; CITRIC ACID MONOHYDRATE; FD&C YELLOW NO. 5; FD&C RED NO. 4

Drug Facts

Active ingredient

chlorhexidine gluconate 0.75% solution

Purposes

Antispetic

Uses

- healthcare personnel handwash: helps reduce bacteria that potentially can cause disease

Warnings

For external use only.

Do not use

- if you are allergic to chlorhexidine gluconate or any other ingredients
- in contact with meninges
- in the genital area
- as a preoperative skin preparation (especially on the head and face)
- on skin wonds
- general skin cleanser as surgical hand scrub

When using this product

- keep out of eyes, ears, and mouth. May cause serious and permanent eye injury if placed or kept in the eye during surgical procedures or may cause deafness when instilled in the middle ear through perforated eardrums.
- if solution should contact these areas, rinse out promptly and thoroughly with water

Stop use and ask a doctor if

irritation, sensitization or allergic reaction occurs. These may be signs of a serious condition.

Keep out of reach of children

If swallowed, get medical help or contact a Poison Control Center right away.

Other safety information

This product contains a chemical known to the State of California to cause Cancer.

Directions

- use with care in premature infants and infants under 2 months of age. These products may cause irritation or chemical burns.

Healthcare personnel handwash:

- wet hands with water
- dispense about 5 ml of product into cupped hands and wash in a vigorous manner for 30 seconds
- rinse and dry thoroughly

Other information

- store at 20-25°C (68-77°F)
- avoid excessive heat above 40°C (104°F)

Inactive ingredients

cocamide DEA, FD&C yellow #5, FD&C red #4, fragrance, hydroxyethylcellulose, isopropyl alcohol, lauramine oxide, purified water, ricinoleamidopropyl trimethyl ammonium chloride

Questions of Comments?

Call 1-855-332-2525 Monday through Friday7:00 AM to 3:30 PM

Package/Label Principal Display Panel

NDC 61037-412-01

SCRUB™

FROM HOSTIPTAL TO HOME

Antiseptic Handwash

Chlorhexidine Gluconate 0.75% Solution

FDA Approved Antiseptic Handwash

Contains: 0.75% Chlorhexidine Gluconate

Distributed by: Bajaj Medical, LLC

415 W. Pershing Rd.,

Chicago, IL 60609

FOR EXTERNAL USE ONLY

Net Contents: 4 fl oz (118 ml)